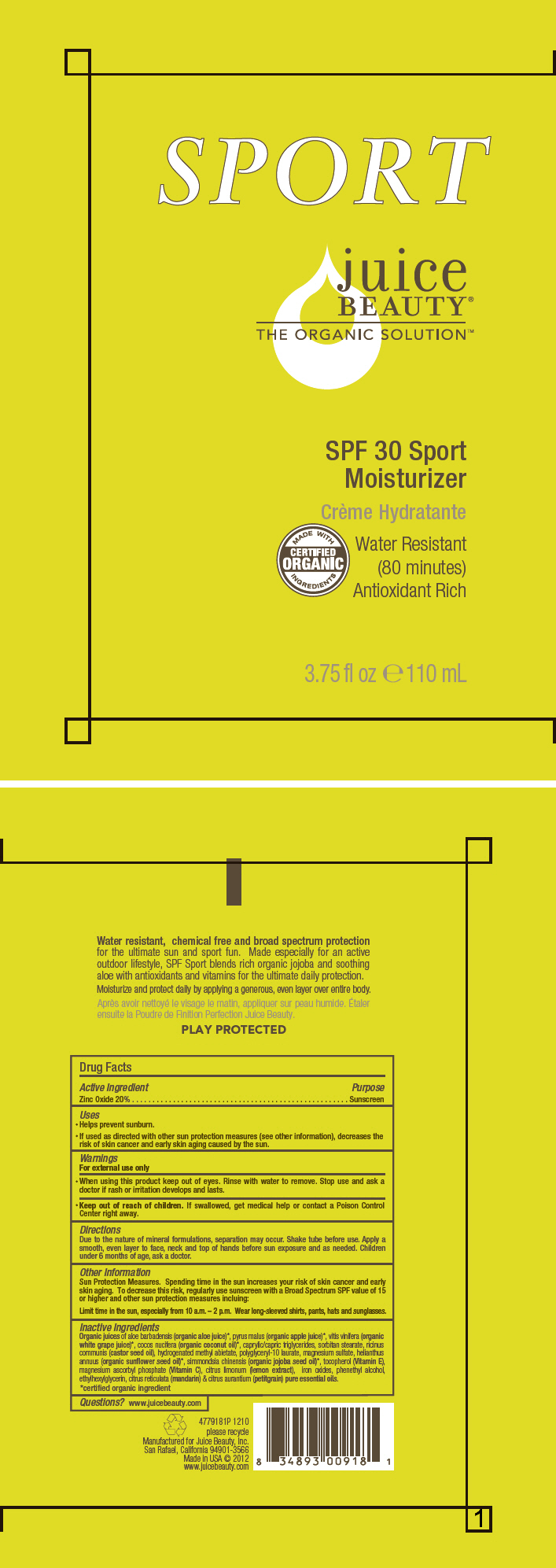 DRUG LABEL: SPF-30 SPORT moisturizer
NDC: 55165-0104 | Form: LOTION
Manufacturer: Juice Beauty
Category: otc | Type: HUMAN OTC DRUG LABEL
Date: 20130905

ACTIVE INGREDIENTS: Zinc Oxide 20 g/100 mL
INACTIVE INGREDIENTS: apple juice; aloe vera leaf; coconut oil; medium-chain triglycerides; sorbitan monostearate; polyglyceryl-10 laurate; magnesium sulfate; sunflower oil; jojoba oil; tocopherol; MAGNESIUM ASCORBYL PHOSPHATE; ferric oxide red; phenylethyl alcohol; ethylhexylglycerin; mandarin oil; citrus aurantium leafy twig oil

SPF-30 SPORT moisturizer

Drug Facts

Active Ingredient

Zinc Oxide 20%

Purpose

Sunscreen

Uses

- Helps prevent sunburn.
- If used as directed with other sun protection measures (see other information), decreases the risk of skin cancer and early skin aging caused by the sun.

Warnings

For external use only

- When using this product keep out of eyes. Rinse with water to remove. Stop use and ask a doctor if rash or irritation develops and lasts.

- Keep out of reach of children. If swallowed, get medical help or contact a Poison Control Center right away.

Directions

Due to the nature of mineral formulations, separation may occur. Shake tube before use. Apply a smooth, even layer to face, neck and top of hands before sun exposure and as needed. Children under 6 months of age, ask a doctor.

Other Information

Sun Protection Measures. Spending time in the sun increases your risk of skin cancer and early skin aging. To decrease this risk, regularly use sunscreen with a Broad Spectrum SPF value of 15 or higher and other sun protection measures incluing:

Limit time in the sun, especially from 10 a.m. – 2 p.m. Wear long-sleeved shirts, pants, hats and sunglasses.

Inactive Ingredients

Organic juices of aloe barbadensis (organic aloe juice) [certified organic ingredient] , pyrus malus (organic apple juice), vitis vinifera (organic white grape juice), cocos nucifera (organic coconut oil), caprylic/capric triglycerides, sorbitan stearate, ricinus communis (castor seed oil), hydrogenated methyl abietate, polyglyceryl-10 laurate, magnesium sulfate, helianthus annuus (organic sunflower seed oil), simmondsia chinensis (organic jojoba seed oil), tocopherol (Vitamin E), magnesium ascorbyl phosphate (Vitamin C), citrus limonum (lemon extract), iron oxides, phenethyl alcohol, ethylhexylglycerin, citrus reticulata (mandarin) & citrus aurantium (petitgrain) pure essential oils.

Questions?

www.juicebeauty.com

PRINCIPAL DISPLAY PANEL - 110 mL Tube Label

SPORT

juice
BEAUTY®
THE ORGANIC SOLUTION™

SPF 30 Sport
Moisturizer

MADE WITH
CERTIFIED
ORGANIC
INGREDIENTS

Water Resistant
(80 minutes)
Antioxidant Rich

3.75 fl oz e 110 mL